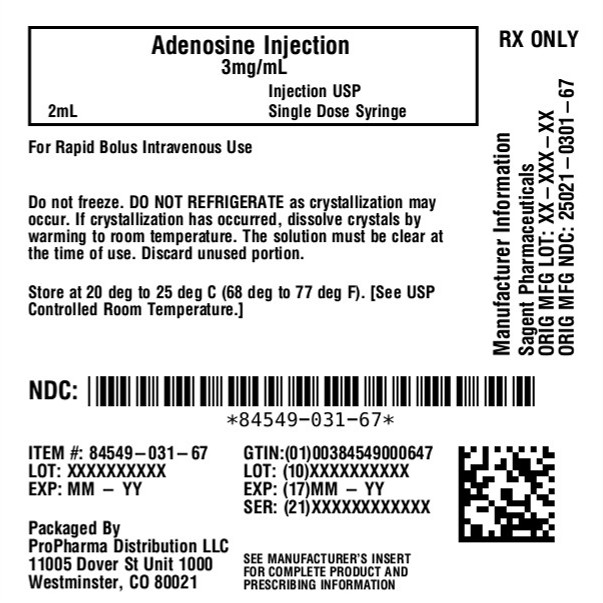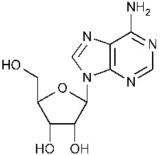 DRUG LABEL: adenosine
NDC: 84549-031 | Form: INJECTION
Manufacturer: ProPharma Distribution
Category: prescription | Type: HUMAN PRESCRIPTION DRUG LABEL
Date: 20260120

ACTIVE INGREDIENTS: ADENOSINE 3 mg/1 mL
INACTIVE INGREDIENTS: SODIUM CHLORIDE; WATER

Adenosine Injection, USP
For Rapid Bolus Intravenous Use

SAGENT™
Rx only

DESCRIPTION

Adenosine is an endogenous nucleoside occurring in all cells of the body. It is chemically 6-amino-9-β-D-ribofuranosyl-9-H-purine and has the following structural formula:

Adenosine is a white crystalline powder. It is soluble in water and practically insoluble in alcohol. Solubility increases by warming and lowering the pH. Adenosine is not chemically related to other antiarrhythmic drugs. Adenosine Injection, USP is a sterile solution for rapid bolus intravenous injection. Each mL contains 3 mg adenosine, USP and 9 mg sodium chloride, USP in water for injection, USP. The pH of the solution is between 4.5 and 7.5.

CLINICAL PHARMACOLOGY

Mechanism of Action

Adenosine slows conduction time through the A-V node, can interrupt the reentry pathways through the A-V node, and can restore normal sinus rhythm in patients with paroxysmal supraventricular tachycardia (PSVT), including PSVT associated with Wolff-Parkinson-White Syndrome.

Adenosine is antagonized competitively by methylxanthines such as caffeine and theophylline, and potentiated by blockers of nucleoside transport such as dipyridamole. Adenosine is not blocked by atropine.

Hemodynamics

The intravenous bolus dose of 6 or 12 mg adenosine usually has no systemic hemodynamic effects. When larger doses are given by infusion, adenosine decreases blood pressure by decreasing peripheral resistance.

Pharmacokinetics

Intravenously administered adenosine is rapidly cleared from the circulation via cellular uptake, primarily by erythrocytes and vascular endothelial cells. This process involves a specific transmembrane nucleoside carrier system that is reversible, nonconcentrative, and bidirectionally symmetrical. Intracellular adenosine is rapidly metabolized either via phosphorylation to adenosine monophosphate by adenosine kinase, or via deamination to inosine by adenosine deaminase in the cytosol. Since adenosine kinase has a lower Kmand Vmaxthan adenosine deaminase, deamination plays a significant role only when cytosolic adenosine saturates the phosphorylation pathway. Inosine formed by deamination of adenosine can leave the cell intact or can be degraded to hypoxanthine, xanthine, and ultimately uric acid. Adenosine monophosphate formed by phosphorylation of adenosine is incorporated into the high-energy phosphate pool. While extracellular adenosine is primarily cleared by cellular uptake with a half-life of less than 10 seconds in whole blood, excessive amounts may be deaminated by an ecto-form of adenosine deaminase. As adenosine requires no hepatic or renal function for its activation or inactivation, hepatic and renal failure would not be expected to alter its effectiveness or tolerability.

Clinical Trial Results

In controlled studies in the United States, bolus doses of 3, 6, 9, and 12 mg were studied. A cumulative 60% of patients with paroxysmal supraventricular tachycardia had converted to normal sinus rhythm within one minute after an intravenous bolus dose of 6 mg adenosine (some converted on 3 mg and failures were given 6 mg), and a cumulative 92% converted after a bolus dose of 12 mg. Seven to sixteen percent of patients converted after 1 to 4 placebo bolus injections. Similar responses were seen in a variety of patient subsets, including those using or not using digoxin, those with Wolff-Parkinson-White Syndrome, males, females, blacks, Caucasians, and Hispanics.

Adenosine is not effective in converting rhythms other than PSVT, such as atrial flutter, atrial fibrillation, or ventricular tachycardia, to normal sinus rhythm.

INDICATIONS AND USAGE

Adenosine Injection, USP is indicated for the following:

Conversion to sinus rhythm of paroxysmal supraventricular tachycardia (PSVT), including that associated with accessory bypass tracts (Wolff-Parkinson-White Syndrome). When clinically advisable, appropriate vagal maneuvers (e.g., Valsalva maneuver), should be attempted prior to adenosine administration.

It is important to be sure the adenosine solution actually reaches the systemic circulation (see DOSAGE AND ADMINISTRATION).

Adenosine does not convert atrial flutter, atrial fibrillation, or ventricular tachycardia to normal sinus rhythm. In the presence of atrial flutter or atrial fibrillation, a transient modest slowing of ventricular response may occur immediately following adenosine administration.

CONTRAINDICATIONS

Adenosine injection is contraindicated in:

1. Second- or third-degree A-V block (except in patients with a functioning artificial pacemaker).
2. Sinus node disease, such as sick sinus syndrome or symptomatic bradycardia (except in patients with a functioning artificial pacemaker).
3. Known hypersensitivity to adenosine.

WARNINGS

Heart Block

Adenosine exerts its effect by decreasing conduction through the A-V node and may produce a short lasting first-, second- or third-degree heart block. Appropriate therapy should be instituted as needed. Patients who develop high-level block on one dose of adenosine should not be given additional doses. Because of the very short half-life of adenosine, these effects are generally self-limiting. Appropriate resuscitative measures should be available.

Transient or prolonged episodes of asystole have been reported with fatal outcomes in some cases. Rarely, ventricular fibrillation has been reported following adenosine administration, including both resuscitated and fatal events. In most instances, these cases were associated with the concomitant use of digoxin and, less frequently with digoxin and verapamil. Although no causal relationship or drug-drug interaction has been established, adenosine should be used with caution in patients receiving digoxin or digoxin and verapamil in combination.

Arrhythmias at Time of Conversion

At the time of conversion to normal sinus rhythm, a variety of new rhythms may appear on the electrocardiogram. They generally last only a few seconds without intervention, and may take the form of premature ventricular contractions, atrial premature contractions, atrial fibrillation, sinus bradycardia, sinus tachycardia, skipped beats, and varying degrees of A-V nodal block. Such findings were seen in 55% of patients.

Bronchoconstriction

Adenosine is a respiratory stimulant (probably through activation of carotid body chemoreceptors) and intravenous administration in man has been shown to increase minute ventilation (Ve) and reduce arterial PCO2causing respiratory alkalosis.

Adenosine administered by inhalation has been reported to cause bronchoconstriction in asthmatic patients, presumably due to mast cell degranulation and histamine release. These effects have not been observed in normal subjects. Adenosine has been administered to a limited number of patients with asthma and mild to moderate exacerbation of their symptoms has been reported. Respiratory compromise has occurred during adenosine infusion in patients with obstructive pulmonary disease. Adenosine should be used with caution in patients with obstructive lung disease not associated with bronchoconstriction (e.g., emphysema, bronchitis, etc.) and should be avoided in patients with bronchoconstriction or bronchospasm (e.g., asthma). Adenosine should be discontinued in any patient who develops severe respiratory difficulties.

PRECAUTIONS

Drug Interactions

Intravenous adenosine has been effectively administered in the presence of other cardioactive drugs, such as quinidine, beta-adrenergic blocking agents, calcium channel blocking agents, and angiotensin converting enzyme inhibitors, without any change in the adverse reaction profile. Digoxin and verapamil use may be rarely associated with ventricular fibrillation when combined with adenosine (see WARNINGS). Because of the potential for additive or synergistic depressant effects on the SA and AV nodes, however, adenosine should be used with caution in the presence of these agents. The use of adenosine in patients receiving digitalis may be rarely associated with ventricular fibrillation (see WARNINGS).

The effects of adenosine are antagonized by methylxanthines such as caffeine and theophylline. In the presence of these methylxanthines, larger doses of adenosine may be required or adenosine may not be effective. Adenosine effects are potentiated by dipyridamole. Thus, smaller doses of adenosine may be effective in the presence of dipyridamole. Carbamazepine has been reported to increase the degree of heart block produced by other agents. As the primary effect of adenosine is to decrease conduction through the A-V node, higher degrees of heart block may be produced in the presence of carbamazepine.

Carcinogenesis, Mutagenesis, Impairment of Fertility

Studies in animals have not been performed to evaluate the carcinogenic potential of adenosine. Adenosine was negative for genotoxic potential in the Salmonella (Ames Test) and Mammalian Microsome Assay.

Adenosine, however, like other nucleosides at millimolar concentrations present for several doubling times of cells in culture, is known to produce a variety of chromosomal alterations. Fertility studies in animals have not been conducted with adenosine.

Pregnancy

Teratogenic Effects: Pregnancy Category C

Animal reproduction studies have not been conducted with adenosine; nor have studies been performed in pregnant women. As adenosine is a naturally occurring material, widely dispersed throughout the body, no fetal effects would be anticipated. However, since it is not known whether adenosine can cause fetal harm when administered to pregnant women, adenosine should be used during pregnancy only if clearly needed.

Pediatric Use

No controlled studies have been conducted in pediatric patients to establish the safety and efficacy of adenosine for the conversion of paroxysmal supraventricular tachycardia (PSVT). However, intravenous adenosine has been used for the treatment of PSVT in neonates, infants, children and adolescents (see DOSAGE AND ADMINISTRATION).^1

Geriatric Use

Clinical studies of adenosine did not include sufficient numbers of subjects aged 65 and over to determine whether they respond differently from younger subjects. Other reported clinical experience has not identified differences in responses between elderly and younger patients. In general, adenosine in geriatric patients should be used with caution since this population may have a diminished cardiac function, nodal dysfunction, concomitant diseases or drug therapy that may alter hemodynamic function and produce severe bradycardia or AV block.

ADVERSE REACTIONS

The following reactions were reported with intravenous adenosine used in controlled U.S. clinical trials. The placebo group had a less than 1% rate of all of these reactions.

Cardiovascular | Facial flushing (18%), headache (2%), sweating, palpitations, chest pain, hypotension (less than 1%).
Respiratory | Shortness of breath/dyspnea (12%), chest pressure (7%), hyperventilation, head pressure (less than 1%).
Central Nervous System | Lightheadedness (2%), dizziness, tingling in arms, numbness (1%), apprehension, blurred vision, burning sensation, heaviness in arms, neck and back pain (less than 1%).
Gastrointestinal | Nausea (3%), metallic taste, tightness in throat, pressure in groin (less than 1%).

Post Marketing Experience (see WARNINGS)

The following adverse events have been reported from marketing experience with adenosine injection. Because these events are reported voluntarily from a population of uncertain size, are associated with concomitant diseases and multiple drug therapies and surgical procedures, it is not always possible to reliably estimate their frequency or establish a causal relationship to drug exposure. Decisions to include these events in labeling are typically based on one or more of the following factors:

(1) seriousness of the event, (2) frequency of the reporting, (3) strength of causal connection to the drug, or a combination of these factors.

Cardiovascular

Prolonged asystole, ventricular tachycardia, ventricular fibrillation, transient increase in blood pressure, bradycardia, atrial fibrillation, and Torsade de Pointes.

Respiratory

Bronchospasm

Central Nervous System

Seizure activity, including tonic clonic (grand mal) seizures, and loss of consciousness.

To report SUSPECTED ADVERSE REACTIONS, contact Sagent Pharmaceuticals, Inc. at 1-866-625-1618 or FDA at 1-800-FDA-1088 orwww.fda.gov/medwatch.

OVERDOSAGE

The half-life of adenosine is less than 10 seconds. Thus, adverse effects are generally rapidly self-limiting. Treatment of any prolonged adverse effects should be individualized and be directed toward the specific effect. Methylxanthines, such as caffeine and theophylline, are competitive antagonists of adenosine.

DOSAGE AND ADMINISTRATION

For rapid bolus intravenous use only.

Adenosine injection should be given as a rapid bolus by the peripheral intravenous route. To be certain the solution reaches the systemic circulation, it should be administered either directly into a vein or, if given into an intravenous line, it should be given as close to the patient as possible and followed by a rapid saline flush.

Adult Patients

The dose recommendation is based on clinical studies with peripheral venous bolus dosing. Central venous (CVP or other) administration of adenosine has not been systematically studied.

The recommended intravenous doses for adults are as follows:

Initial dose:6 mg given as a rapid intravenous bolus (administered over a 1 to 2 second period).

Repeat administration:If the first dose does not result in elimination of the supraventricular tachycardia within 1 to 2 minutes, 12 mg should be given as a rapid intravenous bolus. This 12 mg dose may be repeated a second time if required.

Pediatric Patients

The dosages used in neonates, infants, children and adolescents were equivalent to those administered to adults on a weight basis.

Pediatric Patients with a Body Weight <50 kg

Initial dose:Give 0.05 to 0.1 mg/kg as a rapid intravenous bolus given either centrally or peripherally. A saline flush should follow.

Repeat administration:If conversion of PSVT does not occur within 1 to 2 minutes, additional bolus injections of adenosine can be administered at incrementally higher doses, increasing the amount given by 0.05 to 0.1 mg/kg. Follow each bolus with a saline flush. This process should continue until sinus rhythm is established or a maximum single dose of 0.3 mg/kg is used.

Pediatric Patients with a Body Weight ≥ 50 kg

Administer the adult dose.

Doses greater than 12 mg are not recommended for adult and pediatric patients.

NOTE: Parenteral drug products should be inspected visually for particulate matter and discoloration prior to administration.

HOW SUPPLIED

Adenosine Injection, USP is supplied as a sterile solution in normal saline as follows:

NDC | Adenosine Injection, USP (3 mg per mL)
84549-031-67 | 6 mg per 2 mL in a 2 mL Single-Use Prefilled Plastic Syringe

Storage Conditions

Store at 20° to 25°C (68° to 77°F). [See USP Controlled Room Temperature.]

Do not freeze.

DO NOT REFRIGERATEas crystallization may occur. If crystallization has occurred, dissolve crystals by warming to room temperature. The solution must be clear at the time of use.

Sterile, Nonpyrogenic, Preservative-free, PVC-free, DEHP-free.

The container closure is not made with natural rubber latex.

Discard unused portion.

May require needle or blunt. To prevent needle-stick injuries, needles should not be recapped, purposely bent or broken by hand.

REFERENCE

1. Paul T. Pfammatter. J-P. Adenosine: an effective and safe antiarrhythmic drug in

pediatrics. Pediatric Cardiology 1997; 18:118-126.

Made in India